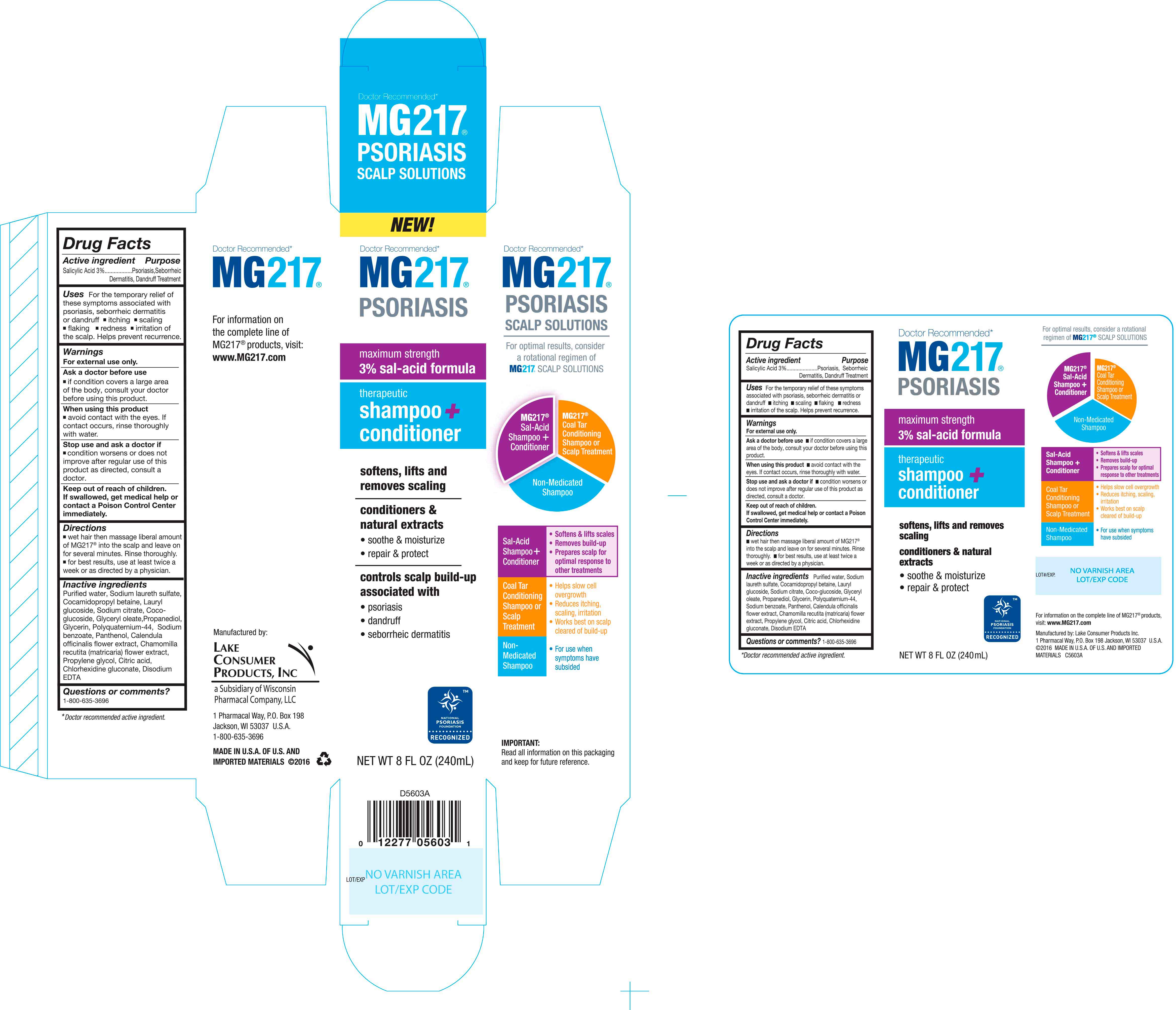 DRUG LABEL: MG217 Psoriasis Therapeutic Conditioner
NDC: 68093-7242 | Form: SHAMPOO
Manufacturer: Wisconsin Pharmacal Company
Category: otc | Type: HUMAN OTC DRUG LABEL
Date: 20160321

ACTIVE INGREDIENTS: SALICYLIC ACID 0.03 g/1 g
INACTIVE INGREDIENTS: SODIUM BENZOATE; CITRIC ACID MONOHYDRATE; CHLORHEXIDINE GLUCONATE; WATER; SODIUM LAURETH SULFATE; COCAMIDOPROPYL BETAINE; SODIUM CITRATE; GLYCERIN; PANTHENOL; CALENDULA OFFICINALIS FLOWER; MATRICARIA CHAMOMILLA FLOWERING TOP OIL; PROPYLENE GLYCOL; EDETATE DISODIUM; LAURYL GLUCOSIDE; COCO GLUCOSIDE; GLYCERYL OLEATE; PROPANEDIOL; POLYQUATERNIUM-44 (200000 MW)

Active Ingredient

Salicylic Acid 3%

Purpose

Psoriasis, Seborrheic Dermatitis, Dandruff Treatment

Uses

For the temporary relief of these symptoms associate with psoriasis, seborrheic dermatitis or dandruff

- itching
- scaling
- flaking,
- reness
- irritaion of the scalp

Helps prevent recurrence.

Warnings

For external use only.

Ask a doctor before use

- if condition covers larger area of body, consult your doctor before using this product.

When using this product

- avoid contact wtih the eyes. If contact occurs, rinse thoroughly with water.

Stop use and ask a doctor if

- condition worsens or does not improve after regular use of this product as directed, consult a doctor.

Keep out of reach of children

If swallowed, get medical help or contact a Poison Control Center Immediately.

Directions

- wet hair then massage liberal amount of MG217 into the scalp and leave on for several minutes. Rinse thoroughly.
- for best results, use at least twice a week or as directed by a physician.

Inactive Ingredients

Purified water, Sodium laureth sulfate, Cocamidopropyl betaine, Lauryl glucoside, Sodium citrate, Coco-glucoside, Glyceryl oleate, Propanediol, Glycerin, Polyquaterinum-44, Sodium benzoate, Panthenol, Calendula officinalis flower extract, Chamomilla recutita (matricaria) flower extract, Propylene glycol, Citric acid, Chlorhexidine gluconate, Disodium EDTA